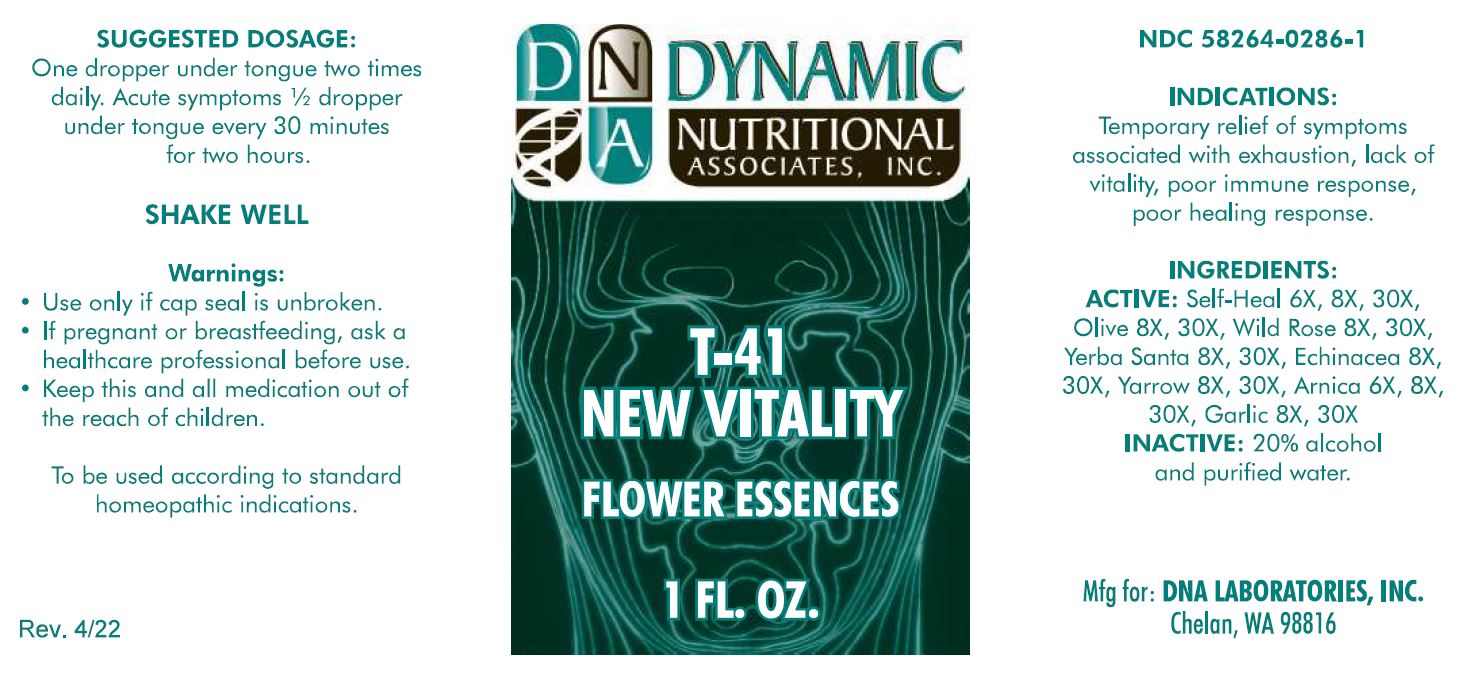 DRUG LABEL: T-41
NDC: 58264-0286 | Form: SOLUTION
Manufacturer: DNA Labs, Inc.
Category: homeopathic | Type: HUMAN OTC DRUG LABEL
Date: 20250109

ACTIVE INGREDIENTS: PRUNELLA VULGARIS FLOWER 30 [hp_X]/1 mL; ROSA CANINA FLOWER 30 [hp_X]/1 mL; ALLIUM SATIVUM WHOLE 30 [hp_X]/1 mL; OLEA EUROPAEA FLOWER 30 [hp_X]/1 mL; ERIODICTYON CALIFORNICUM FLOWERING TOP 30 [hp_X]/1 mL; ACHILLEA MILLEFOLIUM FLOWER 30 [hp_X]/1 mL; ARNICA MONTANA FLOWER 30 [hp_X]/1 mL; ECHINACEA PURPUREA FLOWERING TOP 30 [hp_X]/1 mL
INACTIVE INGREDIENTS: ALCOHOL; WATER

T-41

NDC: 58264-0286-1

INDICATIONS

PURPOSE

Temporary relief of symptoms associated with exhaustion, lack of vitality poor immune response, poor healing response.

INGREDIENTS

Arnica 6X, 8X,30X
Echinacea 8X,30X
Garlic 8X, 30X
Olive 8X, 30X
Self-Heal 6X, 8X, 30X
Wild Rose 8X, 30X
Yarrow 8X, 30X
Yerba Santa 8X, 30X

ACTIVE

Arnica 6X, 8X,30X
Echinacea 8X,30X
Garlic 8X, 30X
Olive 8X, 30X
Self-Heal 6X, 8X, 30X
Wild Rose 8X, 30X
Yarrow 8X, 30X
Yerba Santa 8X, 30X

INACTIVE INGREDIENT

20% alcohol and purified water.

SUGGESTED DOSAGE

One dropper under tongue two times daily. Acute symptoms ½ dropper under tongue every 30 minutes for two hours.

STORAGE AND HANDLING

SHAKE WELL

WARNINGS

Use only if cap seal is unbroken.

PREGNANCY OR BREAST FEEDING

If pregnant or breastfeeding, ask a healthcare professional before use.

KEEP OUT OF REACH OF CHILDREN

Keep this and all medication out of the reach of children.

To be used according to standard homeopathic indications.

PRINCIPAL DISPLAY PANEL - 1 FL. OZ. Bottle Label

DYNAMIC

NUTRITIONAL

ASSOCIATES, INC.

T-41

NEW VITALITY

FLOWER ESSENCES

1 FL. OZ.